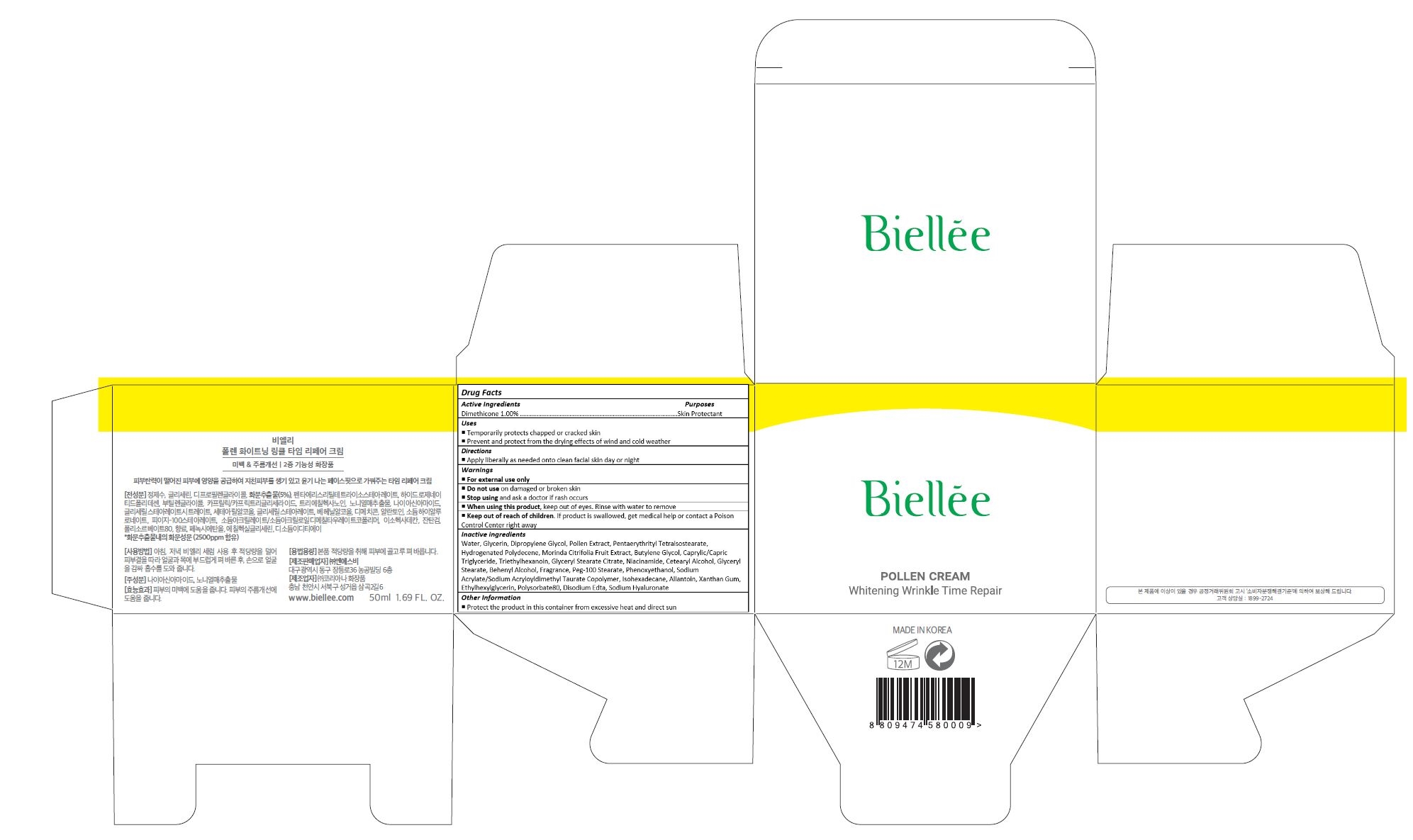 DRUG LABEL: Biellee Pollen Whitening Wrinkle Time Repair Cream
NDC: 70784-002 | Form: CREAM
Manufacturer: NSB CO., LTD.
Category: otc | Type: HUMAN OTC DRUG LABEL
Date: 20160621

ACTIVE INGREDIENTS: DIMETHICONE 0.5 mg/50 mL
INACTIVE INGREDIENTS: WATER; GLYCERIN; DIPROPYLENE GLYCOL; BEE POLLEN; PENTAERYTHRITYL TETRAISOSTEARATE; HYDROGENATED POLYDECENE (550 MW); NONI FRUIT; BUTYLENE GLYCOL; MEDIUM-CHAIN TRIGLYCERIDES; TRIETHYLHEXANOIN; GLYCERYL STEARATE CITRATE; NIACINAMIDE; CETOSTEARYL ALCOHOL; GLYCERYL MONOSTEARATE; DOCOSANOL; PEG-100 STEARATE; PHENOXYETHANOL; SODIUM ACRYLATE/SODIUM ACRYLOYLDIMETHYLTAURATE COPOLYMER (4000000 MW); ISOHEXADECANE; ALLANTOIN; XANTHAN GUM; ETHYLHEXYLGLYCERIN; POLYSORBATE 80; EDETATE DISODIUM; HYALURONATE SODIUM

Drug Facts

ACTIVE INGREDIENT

DIMETHICONE 1.00%

PURPOSE

Skin Protectant

INDICATIONS AND USAGE

Temporarily protects chapped or cracked skin
Prevent and protect from the drying effects of wind and cold weather

DOSAGE AND ADMINISTRATION

Apply liberally as needed onto clean facial skin day or night

WARNINGS

For external use only

Do not use on damaged or broken skin

When using this product, keep out of eyes. Rinse with water to remove.

Stop using and ask a doctor if rash occurs.

KEEP OUT OF REACH OF CHILDREN

Keep out of reach of the children. If product is swallowed, get medical help or contact a poison control center right away.

INACTIVE INGREDIENT

WATER
GLYCERIN
DIPROPYLENE GLYCOL
POLLEN EXTRACT
PENTAERYTHRITYL TETRAISOSTEARATE
HYDROGENATED POLYDECENE
MORINDA CITRIFOLIA FRUIT EXTRACT
BUTYLENE GLYCOL
CAPRYLIC/CAPRIC TRIGLYCERIDE
TRIETHYLHEXANOIN
GLYCERYL STEARATE CITRATE
NIACINAMIDE
CETEARYL ALCOHOL
GLYCERYL STEARATE
BEHENYL ALCOHOL
FRAGRANCE
PEG-100 STEARATE
PHENOXYETHANOL
SODIUM ACRYLATE/SODIUM ACRYLOYLDIMETHYL TAURATE COPOLYMER
ISOHEXADECANE
ALLANTOIN
XANTHAN GUM
ETHYLHEXYLGLYCERIN
POLYSORBATE80
DISODIUM EDTA
SODIUM HYALURONATE